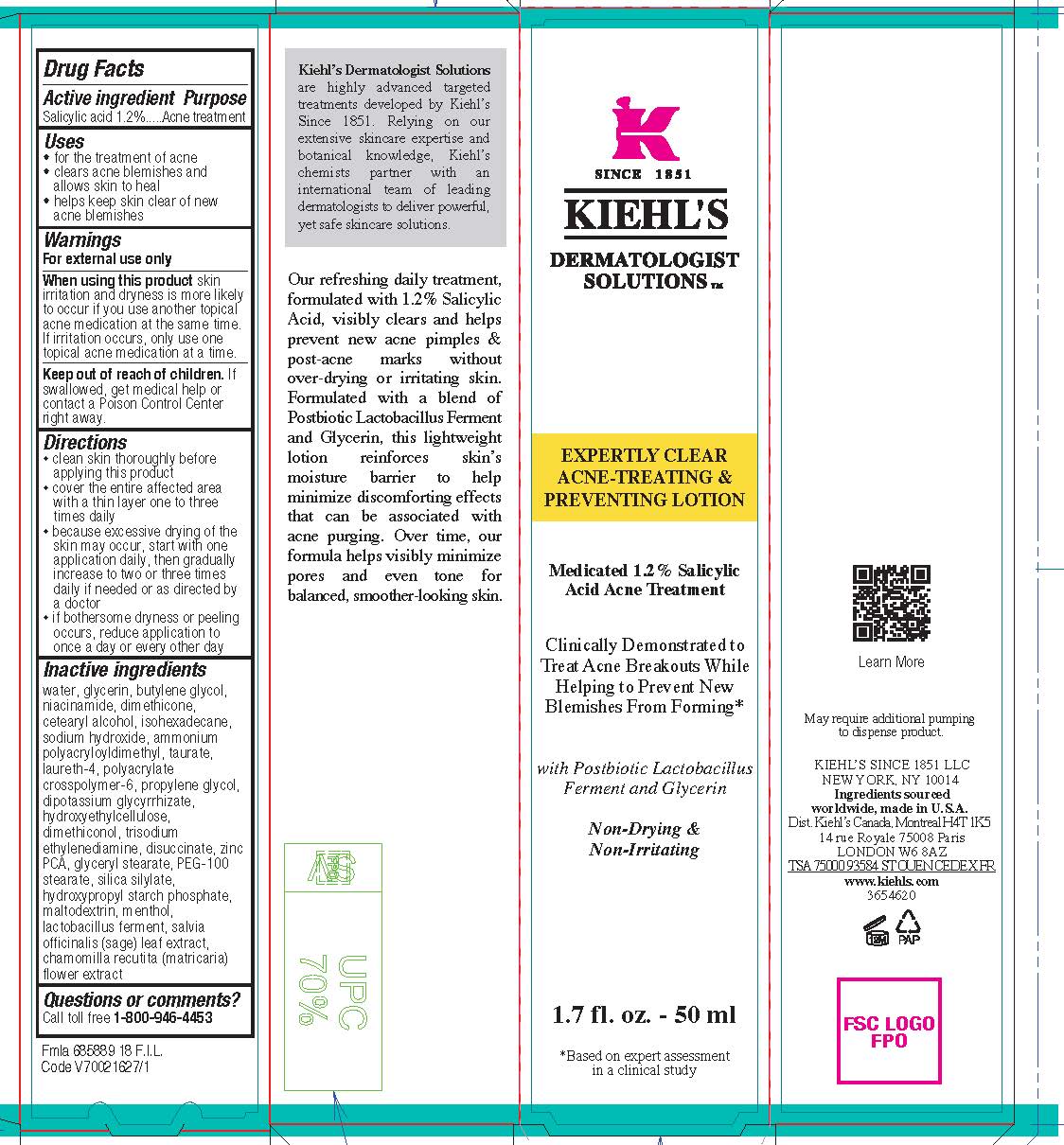 DRUG LABEL: Kiehls Since 1851 Dermatologist Solutions Expertly Clear Acne Treating and Preventing
NDC: 49967-057 | Form: LOTION
Manufacturer: L'Oreal USA Products Inc
Category: otc | Type: HUMAN OTC DRUG LABEL
Date: 20231230

ACTIVE INGREDIENTS: SALICYLIC ACID 12 mg/1 mL
INACTIVE INGREDIENTS: WATER; GLYCERIN; BUTYLENE GLYCOL; NIACINAMIDE; DIMETHICONE; CETOSTEARYL ALCOHOL; ISOHEXADECANE; SODIUM HYDROXIDE; AMMONIUM POLYACRYLOYLDIMETHYL TAURATE; LAURETH-4; AMMONIUM ACRYLOYLDIMETHYLTAURATE, DIMETHYLACRYLAMIDE, LAURYL METHACRYLATE AND LAURETH-4 METHACRYLATE COPOLYMER, TRIMETHYLOLPROPANE TRIACRYLATE CROSSLINKED (45000 MPA.S); PROPYLENE GLYCOL; GLYCYRRHIZINATE DIPOTASSIUM; HYDROXYETHYL CELLULOSE, UNSPECIFIED; DIMETHICONOL (40 CST); TRISODIUM ETHYLENEDIAMINE DISUCCINATE; ZINC PIDOLATE; GLYCERYL MONOSTEARATE; PEG-100 STEARATE; MALTODEXTRIN; MENTHOL; LIMOSILACTOBACILLUS FERMENTUM; SAGE; CHAMOMILE

Drug Facts

Active ingredient

Salicylic acid 1.2%

Purpose

Acne treatment

Uses

- for the treatment of acne
- clears acne blemishes and allows skin to heal
- helps keep skin clear of new acne blemishes

Warnings

For external use only

When using this product

skin irritation and dryness is more likely to occur if you use another topical acne medication at the same time. If irritation occurs, only use one topical acne medication at a time.

Keep out of reach of children.

If swallowed, get medical help or contact a Poison Control Center right away.

Directions

- clean the skin thoroughly before applying this product
- cover the entire affected area with a thin layer one to three times daily
- because excessive drying of the skin may occur, start with one application daily, then gradually increase to two or three times daily if needed or as directed by a doctor
- if bothersome dryness or peeling occurs, reduce application to once a day or every other day

Inactive ingredients

water, glycerin, butylene glycol, niacinamide, dimethicone, cetearyl alcohol, isohexadecane, sodium hydroxide, ammonium polyacryloyldimethyl taurate, laureth-4, polyacrylate crosspolymer-6, propylene glycol, dipotassium glycyrrhizate, hydroxyethylcellulose, dimethiconol, trisodium ethylenediamine disuccinate, zinc PCA, glyceryl stearate, PEG-100 stearate, silica silylate, hydroxypropyl starch phosphate, maltodextrin, menthol, lactobacillus ferment, salvia officinalis (sage) leaf extract, chamomilla recutita (matricaria) flower extract

Questions or comments?

Call toll free 1-800-946-4453